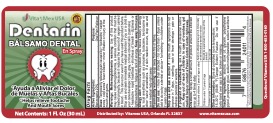 DRUG LABEL: Dentarin
NDC: 69469-200 | Form: SOLUTION
Manufacturer: Vitamex USA, Corp.
Category: otc | Type: HUMAN OTC DRUG LABEL
Date: 20240827

ACTIVE INGREDIENTS: BENZOCAINE 200 mg/1 mL
INACTIVE INGREDIENTS: CLOVE OIL; SACCHARIN SODIUM; PROPYLENE GLYCOL; METHYLPARABEN SODIUM; GLYCERIN; ALCOHOL

Active Ingredients:

Active Ingredients: Purpose

Benzocaine 20%............................... Oral Pain Reliever

Uses:

Uses: Temporarily relieves pain caused by toothache, canker, sores, cold sores, fever blisters, minor irritation or injury of the moth and gums.

Warnings: Methemoglobinemia warning: Use of this product may cause methemoglobinemia, a serious condiiton tha tmust be treated promptly, because it reduces the amount of oxygen carried in blood. This can occur even if you have used this product before. Stop use and seek immediate medical attention if you or a child in your care develops pal, gray, or blue colored skin cyanosis), headache, rapid heartbeat, shortness of breath, diziness or lightheadedness, fatigue or lack of enerygy. Keep away from eyes.

Allergy alert

Allergy alert: do not use this product if you have a history of allergy to local anesthetics such as procaine, butacaine, benzocaine or other "caine" anesthetics. If a skin reaction occurs, stop use and seek medical attention right away.

Flammability warning

Flammability warning: keep away from fire or flame

Do not use: more than directed, for more than 7 days unless told to do so by a dentist or doctor, for teething, in children under 2 years of age.

Stop use and ask a doctor if: sore mouth symptoms do not improve in 7 days, swelling, rash or fever develops, pain or redness persists or worsens.

If pregnant or breastfeeding, ask a health professional before use

Keep out of reach of children

keep out of rech of children. In case of overdose, get medical help or contact a Poison Control Center right away.

Directions:

Adults and children 2 years of age older | Apply to affected area up to 4 times daily or as directed by dentist or doctor

Children under 12 years of age | Should be supervised in the use of this product

Children under 2 years of age | Do not use

Directions: Spray a small amount of product around the affected area up to 4 times daily.

Other information

Other information: Store at controlled room temperature: 15-30ºC (59-86ºF). Tamper Evident Feature: Do not use if cello-band over cap is torn, broken or missing.

Inactive ingredients

Inactive ingredients: alcohol, clove oil, glycerin, polyethylene glycol, propylene glycol, sodium methylparaben, sodium saccharin

Change in section type from directions to indications and useage

Doseage and administration

Adults and children 2 years of age older | Apply to affected area up to 4 times daily or as directed by dentist or doctor
Children under 12 years of age | Should be supervised in the use of this product
Children under 2 years of age | Do not use

Directions: Spray a small amount of product around the affected area up to 4 times daily.

Dentarin

Balsamo Dental En Spray

Helps relieve Toothache and Mouth Sores

Net Contents: 1 Fl. Oz (30mL)